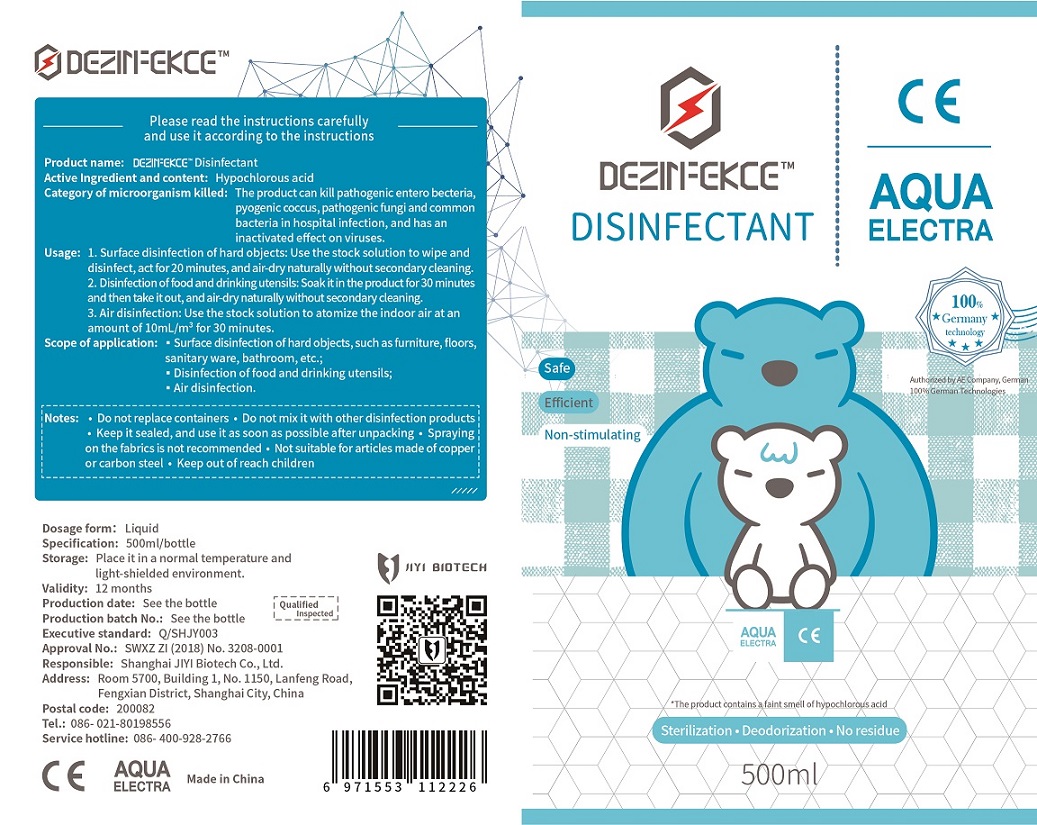 DRUG LABEL: DEZINFEKCE Disinfectant
NDC: 75316-115 | Form: LIQUID
Manufacturer: Shanghai Jiyi Biological Technology Co., Ltd.
Category: otc | Type: HUMAN OTC DRUG LABEL
Date: 20200423

ACTIVE INGREDIENTS: HYPOCHLOROUS ACID 350 mg/500 mL
INACTIVE INGREDIENTS: WATER; SODIUM CHLORIDE

JiYi, DEZINFEKCE Disinfectant, Liquid, 500mL

Active Ingredient(s)

Hypochlorous acid 700 mg/L. Purpose: Kill microorganism.

Purpose

The product can kill pathogenic entero becteria, pyogenic coccus, pathogenic fungi and common bacteria in hospital infection, and has an inactivated effect on viruses.

Use

1. Surface disinfection of hard objects: Use the stock solution to wipe and disinfect, act for 20 minutes, and air-dry naturally without secondary cleaning.

2. Disinfection of food and drinking utensils: Soak it in the product for 30 minutes and then take it out, and air-dry naturally without secondary cleaning.

3. Air disinfection: Use the stock solution to atomize the indoor air at an amount of 10mL/m3 for 30 minutes.

Scope of application: surface disinfection of hard objects, such as furniture, floors, sanitary ware, bathroom, etc.; and drinking utensils; Air disinfection.

Warnings

External Use Only

•Do not replace containers

•Do not mix it with other disinfection products

•Keep it sealed, and use it as soon as possible after unpacking

•Spraying on the fabrics is not recommended

•Not suitable for articles made of copper or carbon steel

•Keep out of reach children

Do not use

- on children less than 2 months of age
- on open skin wounds
- mixing this product with other disinfectants

When using this product keep out of eyes, ears, and mouth.

In case of contact with eyes, rinse eyes thoroughly with water.

This product is for external use. It should not be taken orally.

This product has a certain corrosive effect on metal objects other than stainless steel, and should be used with caution.

When sterilizing articles containing more organic objects, they should be completely removed and then disinfected.

Use with caution for those with sensitive skin.

Do not mix this product with other disinfectants.

Stop use and ask a doctor if irritation or rash occurs. These may be signs of a serious condition.

Directions

1. Surface disinfection of hard objects: Use the stock solution to wipe and disinfect, act for 20 minutes, and air-dry naturally without secondary cleaning.

2. Disinfection of food and drinking utensils: Soak it in the product for 30 minutes and then take it out, and air-dry naturally without secondary cleaning.

3. Air disinfection: Use the stock solution to atomize the indoor air at an amount of 10mL/m3 for 30 minutes.

Other information

Storage: place it in a normal temperature and light-shielded environment.

Inactive ingredients

Sodium chloride, Water